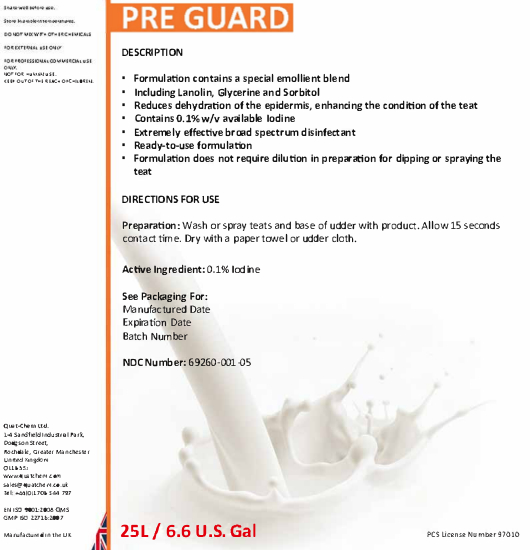 DRUG LABEL: Pre Guard
NDC: 69260-001 | Form: LIQUID
Manufacturer: Quat-Chem Ltd.
Category: animal | Type: OTC ANIMAL DRUG LABEL
Date: 20160316

ACTIVE INGREDIENTS: IODINE 2 g/1 L

Pre Guard

Pre Guard

Shake well before use.
Store in ambient temperatures.
DO NOT MIX WITH OTHER CHEMICALS
FOR EXTERNAL USE ONLY
FOR PROFESSIONAL COMMERCIAL USE
ONLY.
NOT FOR HUMAN USE.
KEEP OUT OF THE REACH OF CHILDREN.

DESCRIPTION
▪ Formulation contains a special emollient blend
▪ Including Lanolin, Glycerine and Sorbitol
▪ Reduces dehydration of the epidermis, enhancing the condition of the teat
▪ Contains 0.1% w/v available Iodine
▪ Extremely effective broad spectrum disinfectant
▪ Ready-to-use formulation
▪ Formulation does not require dilution in preparation for dipping or spraying the
teat

DIRECTIONS FOR USE
Preparation: Wash or spray teats and base of udder with product. Allow 15 seconds
contact time. Dry with a paper towel or udder cloth.

Active Ingredient: 0.1% Iodine

See Packaging For:
Manufactured Date
Expiration Date
Batch Number

NDC Number: